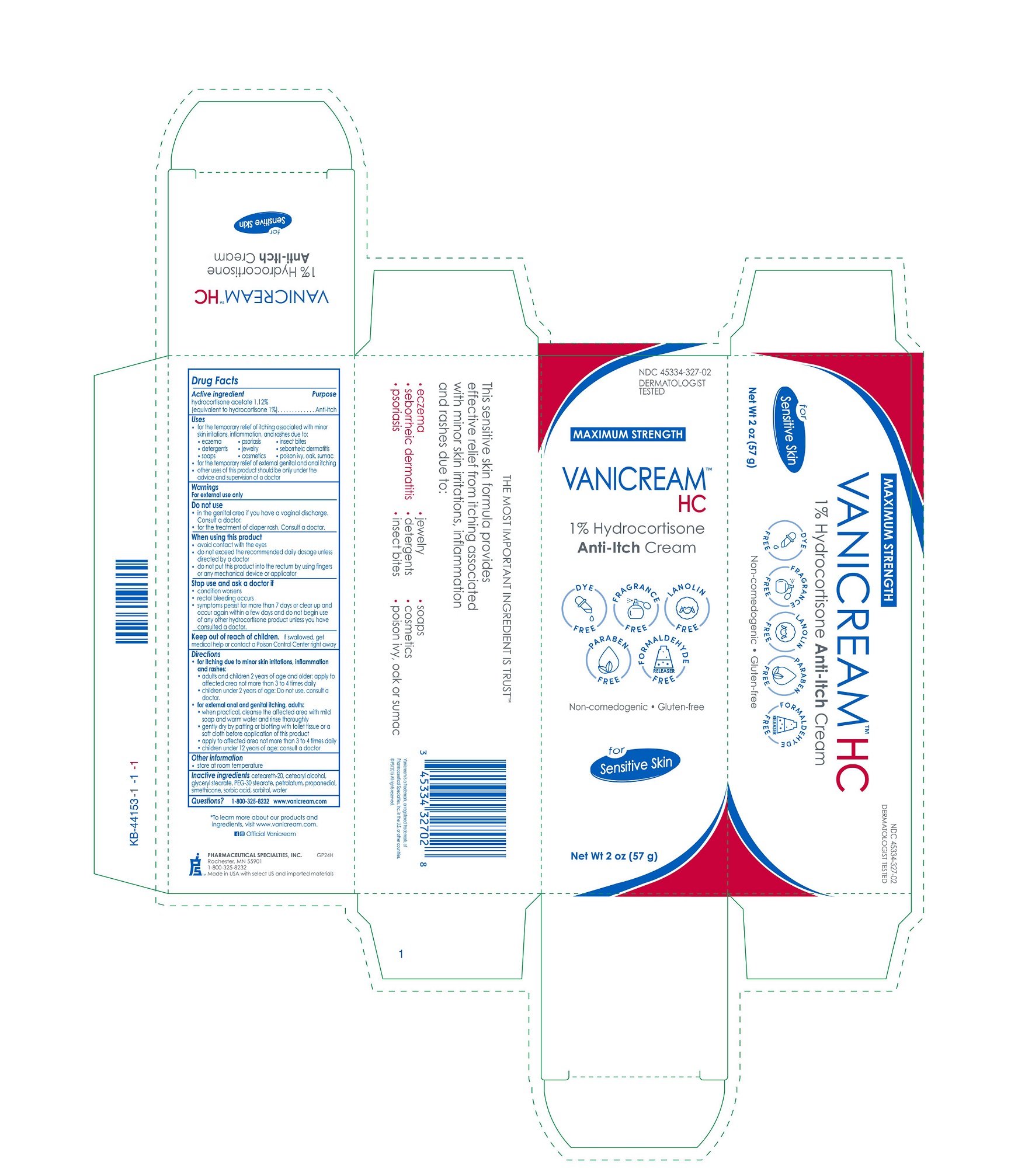 DRUG LABEL: Vanicream HC Anti-Itch
NDC: 45334-327 | Form: CREAM
Manufacturer: Pharmaceutical Specialties, Inc.
Category: otc | Type: HUMAN OTC DRUG LABEL
Date: 20251014

ACTIVE INGREDIENTS: HYDROCORTISONE ACETATE 1.12 g/100 g
INACTIVE INGREDIENTS: PETROLATUM; CETOSTEARYL ALCOHOL; SORBIC ACID; POLYOXYL 20 CETOSTEARYL ETHER; PEG-30 STEARATE; PROPANEDIOL; SORBITOL; GLYCERYL MONOSTEARATE; WATER; SILICON DIOXIDE; DIMETHICONE

VANICREAM™ HC Anti-Itch Cream

Active ingredient

Hydrocortisone acetate 1.12%

(equivalent to hydrocortisone 1%)

Purpose

Anti-itch

Uses

- for the temporary relief of itching associated with minor skin irritations, inflammation and rashes due to:

· eczema · psoriasis · insect bites

· detergents · jewelry · seborrheic dermatitis

· soaps · cosmetics · poison ivy, oak, sumac

- for the temporary relief of external genital and anal itching
- other uses of this product should be only under the advice and supervision of a doctor

Warnings

For external use only

Do not use

- in the genital area if you have a vaginal discharge. Consult a doctor.
- for the treatment of diaper rash. Consult a doctor.

When using this product

- avoid contact with the eyes
- do not exceed the recommended daily dosage unless directed by a doctor
- do not put this product into the rectum by using fingers or any mechanical device or applicator

Stop use and ask a doctor if

- condition worsens
- rectal bleeding occurs
- symptoms persist for more than 7 days or clear up and occur again within a few days and do not begin use of any other hydrocortisone product unless you have consulted a doctor.

Keep out of reach of children. If swallowed, get medical help or contact a Poison Control Center right away

Directions

- for itching due to minor skin irritations, inflammation and rashes:
- adults and children 2 years of age and older: apply to affected area not more than 3 to 4 times daily
- children under 2 years of age: Do not use, consult a doctor.

- for external anal and genital itching, adults:
- when practical, cleanse the affected area with mild soap and warm water and rinse thoroughly
- gently dry by patting or blotting with toilet tissue or a soft cloth before application of this product
- apply to affected area not more than 3 to 4 times daily
- children under 12 years of age: consult a doctor

Other information

- store at room temperature

INACTIVE INGREDIENT

Inactive ingredients ceteareth-20, cetearyl alcohol, glyceryl stearate, PEG-30 stearate, petrolatum, propanediol, simethicone, sorbic acid, sorbitol, water

Questions?

1-800-325-8232

www.vanicream.com

*To learn more about our products and ingredients, visit www.vanicream.com

facebook logo, instagram logo Official Vanicream

PHARMACEUTICAL SPECIALTIES, INC.

ROCHESTER, MN 55901

1-800-325-8232

Made in USA with select US and imported materials

GP24H

Vanicream is a trademark, or registered trademark, of Pharmaceutical Specialties, Inc. in the U.S. or other countries.

© PSI 2015 All rights reserved

PACKAGE LABEL

NDC 45334-327-02

DERMATOLOGIST TESTED

MAXIMUM STRENGTH

VANICREAM™ HC

1% Hydrocortisone Anti-Itch Cream

Non-comedogenic ● Gluten-Free

for Sensitive Kin

Net Wt 2 oz (57 g)